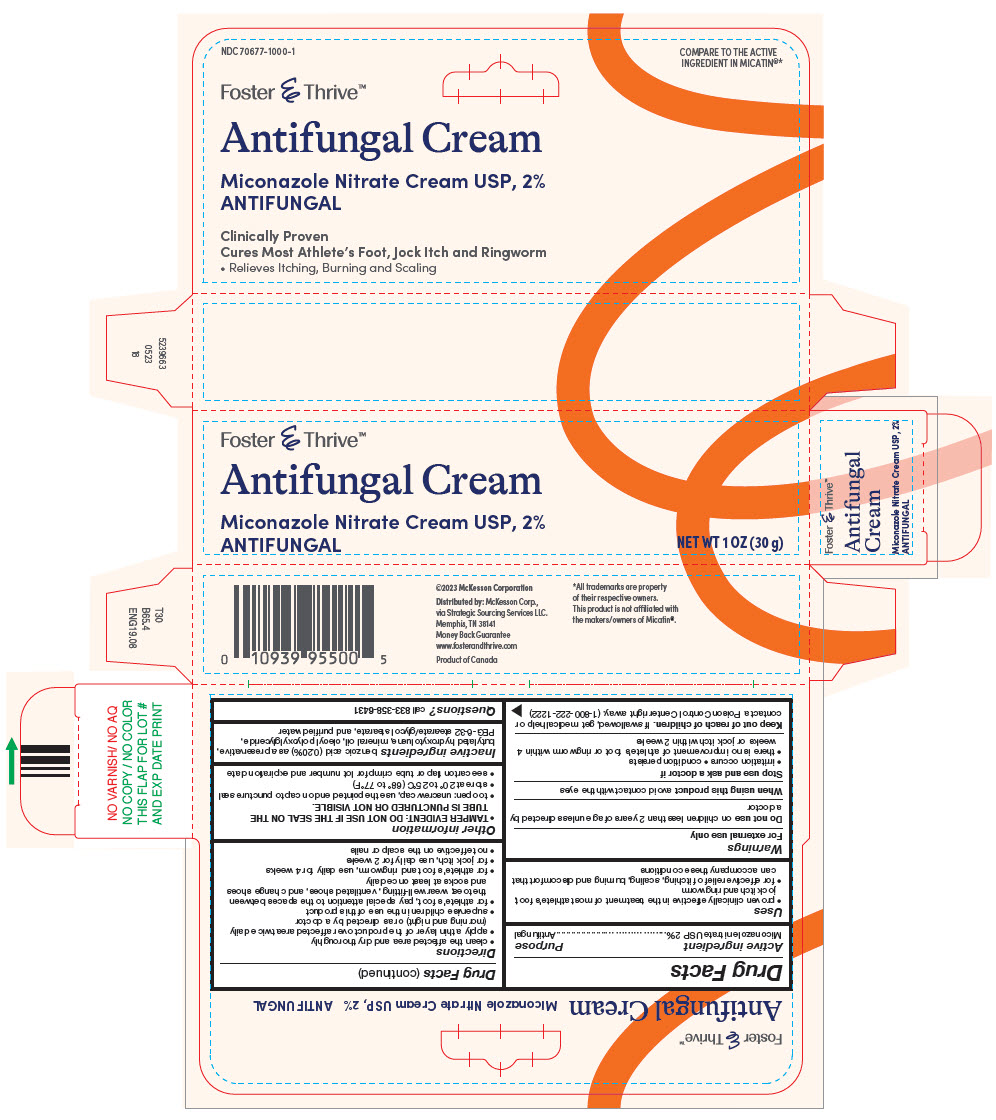 DRUG LABEL: Miconazole Nitrate
NDC: 70677-1000 | Form: CREAM
Manufacturer: STRATEGIC SOURCING SERVICES LLC
Category: otc | Type: HUMAN OTC DRUG LABEL
Date: 20250715

ACTIVE INGREDIENTS: MICONAZOLE NITRATE 20 mg/1 g
INACTIVE INGREDIENTS: BENZOIC ACID; BUTYLATED HYDROXYTOLUENE; MINERAL OIL; PEG-7 LINOLEOYL GLYCERIDES; GLYCOL STEARATE; WATER

Miconazole Nitrate

Drug Facts

Active ingredient

Miconazole nitrate USP 2%

Purpose

Antifungal

Uses

- proven clinically effective in the treatment of most athlete's foot, jock itch and ringworm
- for effective relief of itching, scaling, burning and discomfort that can accompany these conditions

Warnings

For external use only

DO NOT USE

Do not useon children less than 2 years of age unless directed by a doctor

When using this productavoid contact with the eyes

Stop use and ask a doctor if

- irritation occurs
- condition persists
- there is no improvement of athlete's foot or ringworm within 4 weeks or jock itch within 2 weeks

Keep out of reach of children.If swallowed, get medical help or contact a Poison Control Center right away. (1-800-222-1222)

Directions

- clean the affected area and dry thoroughly
- apply a thin layer of the product over affected area twice daily (morning and night) or as directed by a doctor
- supervise children in the use of this product
- for athlete's foot, pay special attention to the spaces between the toes; wear well-fitting, ventilated shoes, and change shoes and socks at least once daily
- for athlete's foot and ringworm, use daily for 4 weeks
- for jock itch, use daily for 2 weeks
- not effective on the scalp or nails

Other information

- TAMPER EVIDENT: DO NOT USE IF THE SEAL ON THE TUBE IS PUNCTURED OR NOT VISIBLE.
- to open: unscrew cap, use the pointed end on cap to puncture seal
- store at 20° to 25°C (68° to 77°F)
- see carton flap or tube crimp for lot number and expiration date

Inactive ingredients

benzoic acid (0.20%) as a preservative, butylated hydroxytoluene, mineral oil, oleoyl polyoxylglyceride, PEG-6-32 stearate/glycol stearate, and purified water

Questions?

call 833-358-6431

Distributed by:McKesson Corp.,
via Strategic Sourcing Services LLC.
Memphis, TN 38141

PRINCIPAL DISPLAY PANEL - 30 g Tube Carton

Foster & Thrive™

Antifungal Cream

Miconazole Nitrate Cream USP, 2%
ANTIFUNGAL

NET WT 1 OZ (30 g)